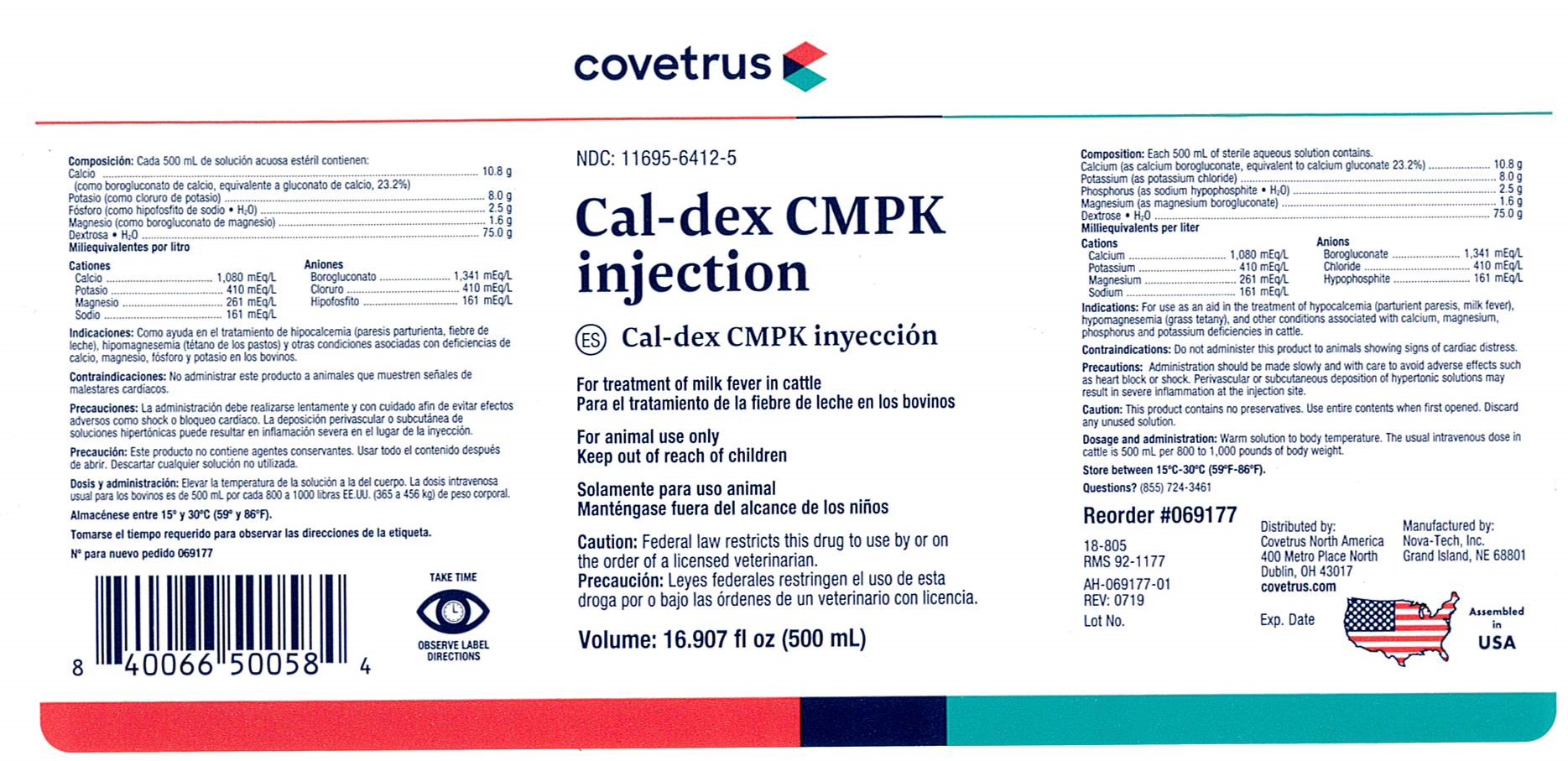 DRUG LABEL: Cal-dex CMPK
NDC: 11695-6412 | Form: INJECTION, SOLUTION
Manufacturer: Covetrus
Category: animal | Type: PRESCRIPTION ANIMAL DRUG LABEL
Date: 20200317

ACTIVE INGREDIENTS: Dextrose monohydrate 75.0 g/500 mL; Potassium Chloride 8.0 g/500 mL; Calcium Gluconate Monohydrate 10.8 g/500 mL; Phosphorus 2.5 g/500 mL; Magnesium Gluconate 1.6 g/500 mL

Cal-dex CMPK

COMPOSITION:

Each 500 mL of sterile aqueous solution contains.
Calcium (as calcium borogluconate, equivalent to calcium gluconate 23.2%) .............. 10.8 g
Potassium (as potassium chloride) ........................................................................ 8.0 g
Phosphorus (as sodium hypophosphite • H2O) .......................................................... 2.5 g
Magnesium (as magnesium borogluconate) ............................................................ 1.6 g
Dextrose • H2O .................................................................................................... 75.0 g
MILLIEQUIVALENTS PER LITER

Cations
Calcium ................ 1,080 mEq/L
Potassium ............... 410 mEq/L
Magnesium ............. 261 mEq/L
Sodium .................. 161 mEq/L

Anions
Borogluconate ....... 1,341 mEq/L
Chloride .................. 410 mEq/L
Hypophosphite ......... 161 mEq/L

INDICATIONS:

For use as an aid in the treatment of hypocalcemia (parturient paresis, milk
fever), hypomagnesemia (grass tetany), and other conditions associated with calcium,
magnesium, phosphorus and potassium deficiencies in cattle.

CONTRAINDICATIONS:

Do not administer this product to animals showing signs of cardiac
distress.

PRECAUTIONS:

Administration should be made slowly and with care to avoid adverse
effects such as heart block or shock. Perivascular or subcutaneous deposition of hypertonic
solutions may result in severe inflammation at the injection site.

CAUTION:

This product contains no preservatives. Use entire contents when first opened.
Discard any unused solution.

DOSAGE AND ADMINISTRATION:

Warm solution to body temperature. The usual
intravenous dose in cattle is 500 mL per 800 to 1,000 pounds of body weight.

STORAGE AND HANDLING

Store between 15°C - 30°C (59°F - 86°F).

WARNINGS AND PRECAUTIONS

TAKE TIME OBSERVE LABEL DIRECTIONS

Keep Out of Reach of Children

VETERINARY INDICATIONS

For Animal Use Only

CAUTION:

Federal law restricts this drug to use by or on
the order of a licensed veterinarian.

INFORMATION FOR OWNERS/CAREGIVERS

NDC: 11695-6412-5

For treatment of milk fever in cattle

Volume: 16.907 fl oz (500 mL)

Questions? (855) 724-3461

Reorder #069177

18-805

RMS 92-1177

AH-069177-01

REV: 0719

Lot No.

Exp. Date

Distributed by:

Covetrus North America

400 Metro Place North

Dublin, OH 43017

covetrus.com

Manufactued by:

Nova-Tech, Inc.

Grand Island, NE 68801

Assembled in USA